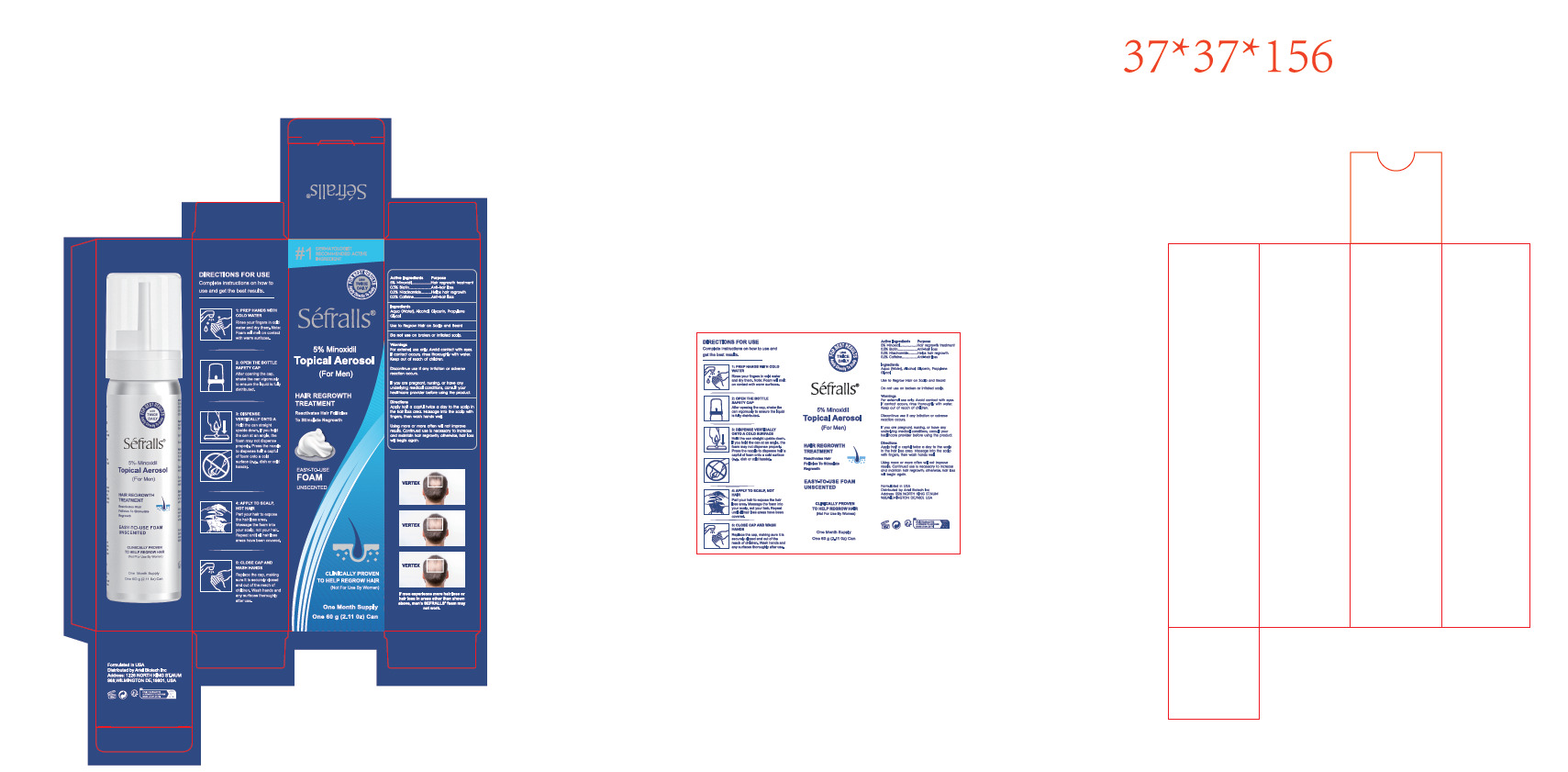 DRUG LABEL: 5% Minoxidil Hair Growth Foam
NDC: 84148-013 | Form: LIQUID
Manufacturer: Guangzhou Ariel Biotech Co., Ltd.
Category: otc | Type: HUMAN OTC DRUG LABEL
Date: 20250415

ACTIVE INGREDIENTS: MINOXIDIL 5 g/100 g; NIACINAMIDE 0.2 g/100 g; CAFFEINE 0.2 g/100 g; BIOTIN 0.3 g/100 g
INACTIVE INGREDIENTS: ROSEMARY; AQUA; ALCOHOL; PROPYLENE GLYCOL; GLYCERIN; SODIUM LAURYL GLYCOL CARBOXYLATE

84148-013
5% Minoxidil Hair Growth Foam

Active Ingredient(s)

5% Minoxidil.
0.3% Biotin.
0.2% Niacinamide..
0.2% Caffeine.

Purpose

Hair regrowth treatment
Anti-hair loss
Helps hair regrowth
Anti-hair loss

Use

Use to Regrow Hair on Scalp and Beard

Warnings

1. For external use only. Avoid contact with eyes. If contact occurs, rinse thoroughly with water.
Keep out of reach of children.

2. Discontinue use if any rritation or adverse reaction occurs.
3. If you are pregnant, nursing, or have any underlying medical conditions, consult your
healthcare provider before using the product.

Do not use on broken or irritated scalp.

WHEN USING

Discontinue use if any rritation or adverse reaction occurs.

For external use only. Avoid contact with eyes.

If contact occurs, rinse thoroughly with water.

Keep out of reach of children.

Directions

1. Apply half a capful twice a day to the scalp in the hair loss area. Massage into the scalp with
fingers, then wash hands well.
2. Using more or more often will not improve results. Continued use is necessary to increase
and maintain hair regrowth; otherwise, hair loss will begin again.

Other information

No Data

Inactive ingredients

Aqua (Water), Alcohol, Glycerin, Propylene Glycol